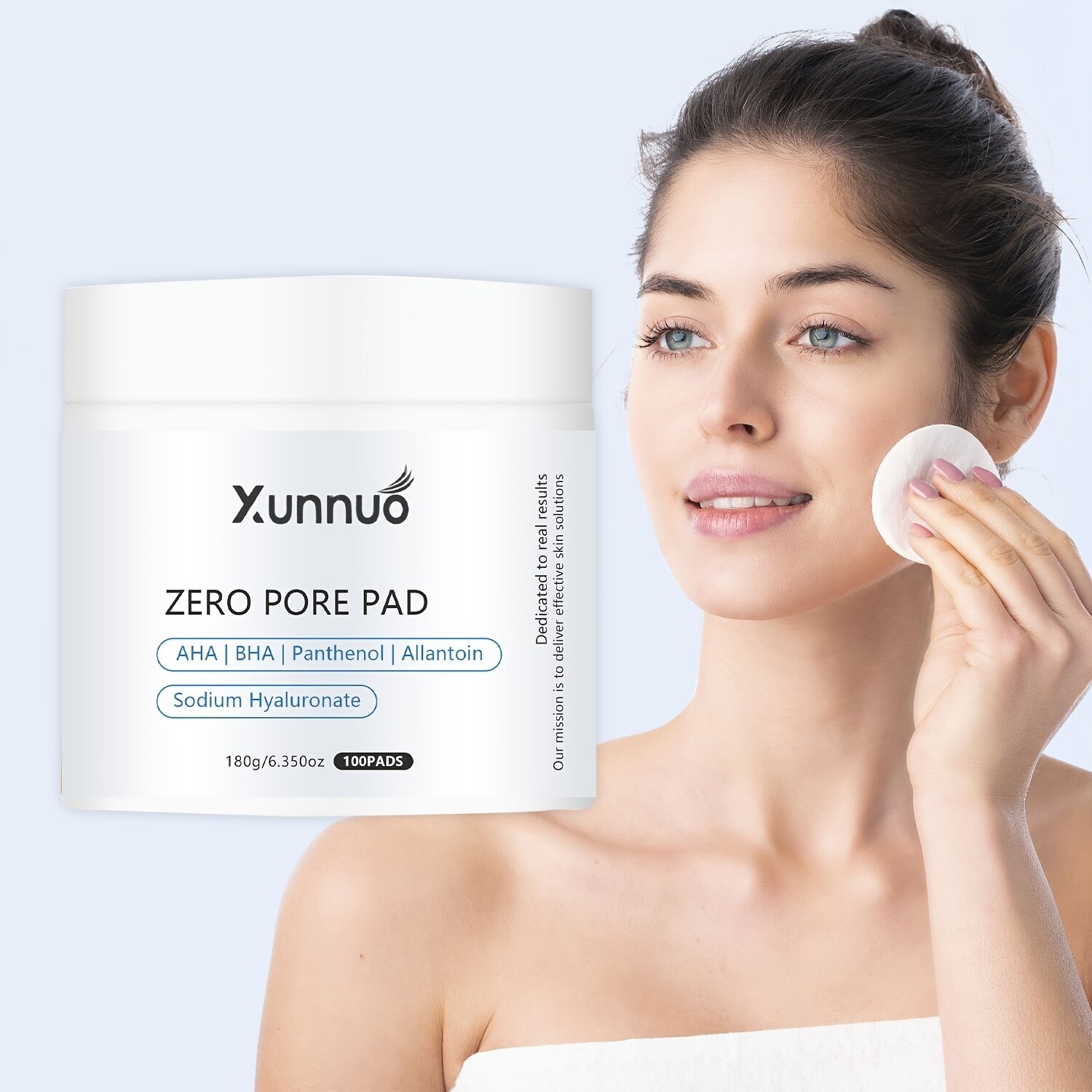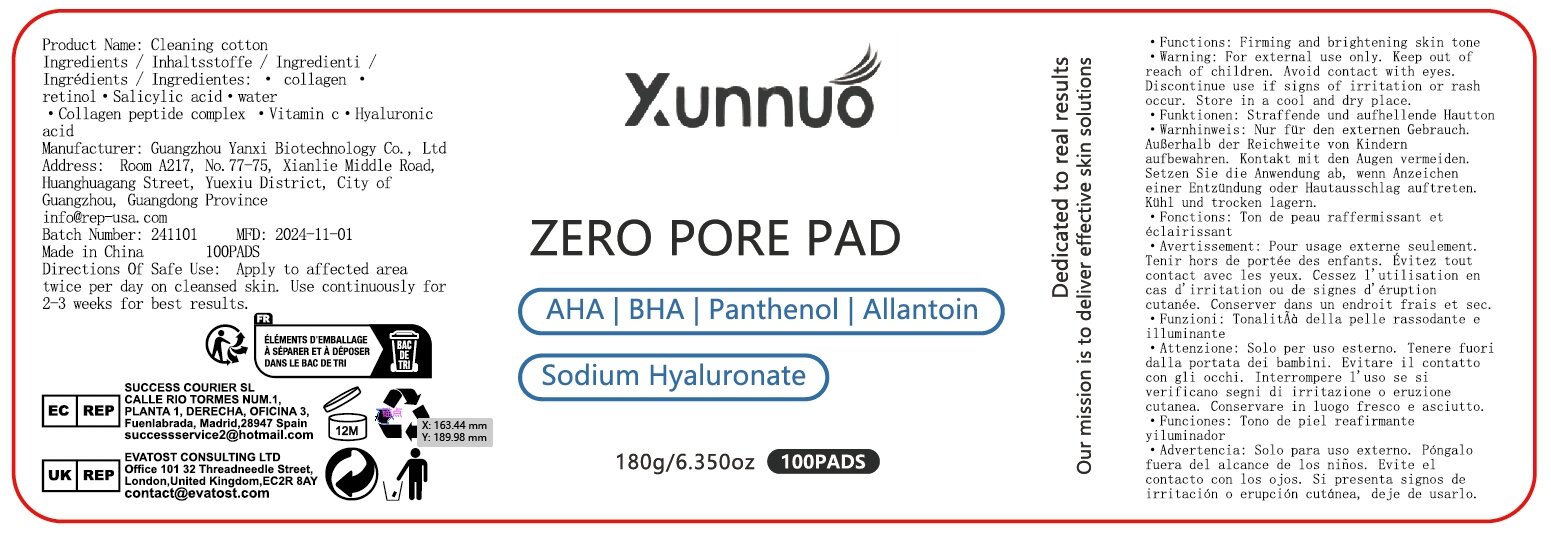 DRUG LABEL: Cleaning cotton
NDC: 84025-295 | Form: SWAB
Manufacturer: Guangzhou Yanxi Biotechnology Co., Ltd
Category: otc | Type: HUMAN OTC DRUG LABEL
Date: 20241223

ACTIVE INGREDIENTS: RETINOL 5 mg/100 g; HYALURONIC ACID 3 mg/100 g
INACTIVE INGREDIENTS: WATER

DOSAGE AND ADMINISTRATION

use as a normal face clean

WARNINGS

keep out of children

INACTIVE INGREDIENT

Aqua

INDICATIONS AND USAGE

for daily face care

keep out of children

PURPOSE

Clean and hydrate the face